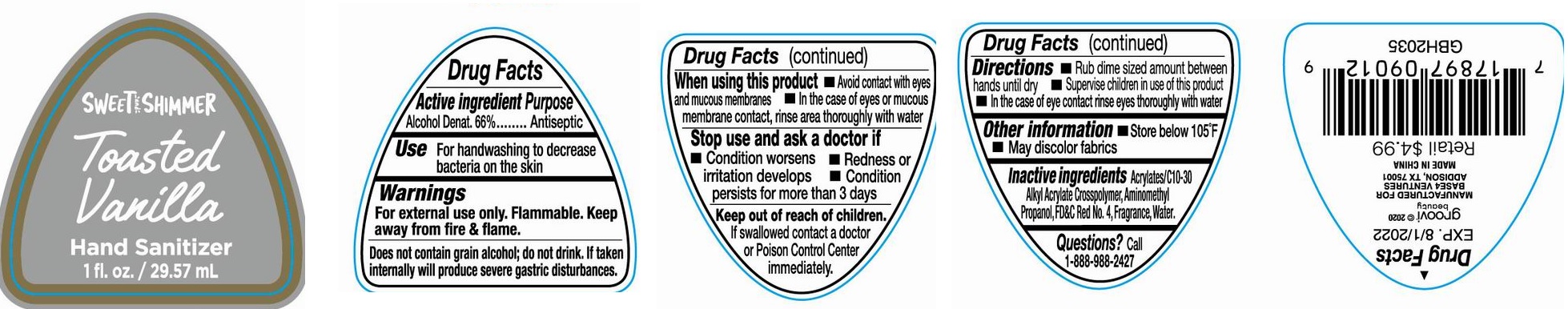 DRUG LABEL: Sweet Shimmer Hand Sanitizer Toasted Vanilla
NDC: 56136-341 | Form: GEL
Manufacturer: Ganzhou Olivee Cosmetic Co., Ltd.
Category: otc | Type: HUMAN OTC DRUG LABEL
Date: 20200627

ACTIVE INGREDIENTS: ALCOHOL 66 mL/100 mL
INACTIVE INGREDIENTS: WATER; CARBOMER COPOLYMER TYPE A; AMINOMETHYLPROPANOL; FD&C RED NO. 4

HAND SANITIZER

Active ingredient

Alcohol Denat. 66%

Purpose

Antiseptic

Use

For handwashing to decreases bacteria on skin

Warnings

For external use only.

Flammable. Keep product away from fire or flame.

When using this product avoid contact with eyes and mucous membranes. In case of eyes or mucous membrane contact, rinse area thoroughly with water.

Stop use and ask a doctor if Condition worsens, redness or irritation develops, condition persists for more than 3 days

Does not contain grain alcoho; do not drink. If taken internally will produce severe gastric disturbances.

Other information

- Store below 105℉
- May discolor fabrics

Keep out of reach of children.

If swallowed, get medical help or contact a Poison Control Center right away.

Directions

- rub dime sized amount between hands until dry
- Supervise children in use of this product
- In the case of eye contact rinse eyes thoroughly with water

Inactive ingredients

Acrylates/C10-30 Alkyl Acrylate Crosspolymer, Aminomethyl Propanol, FD&C Red No. 4Fragrance, water.